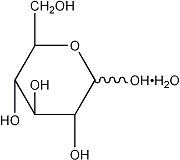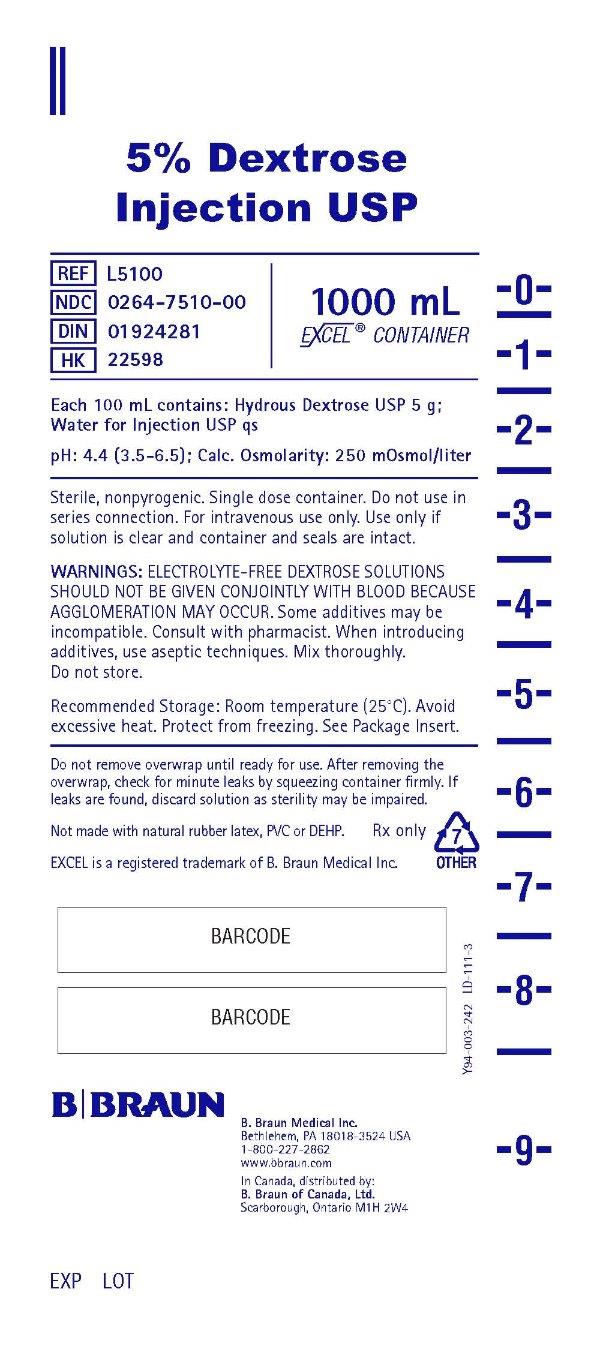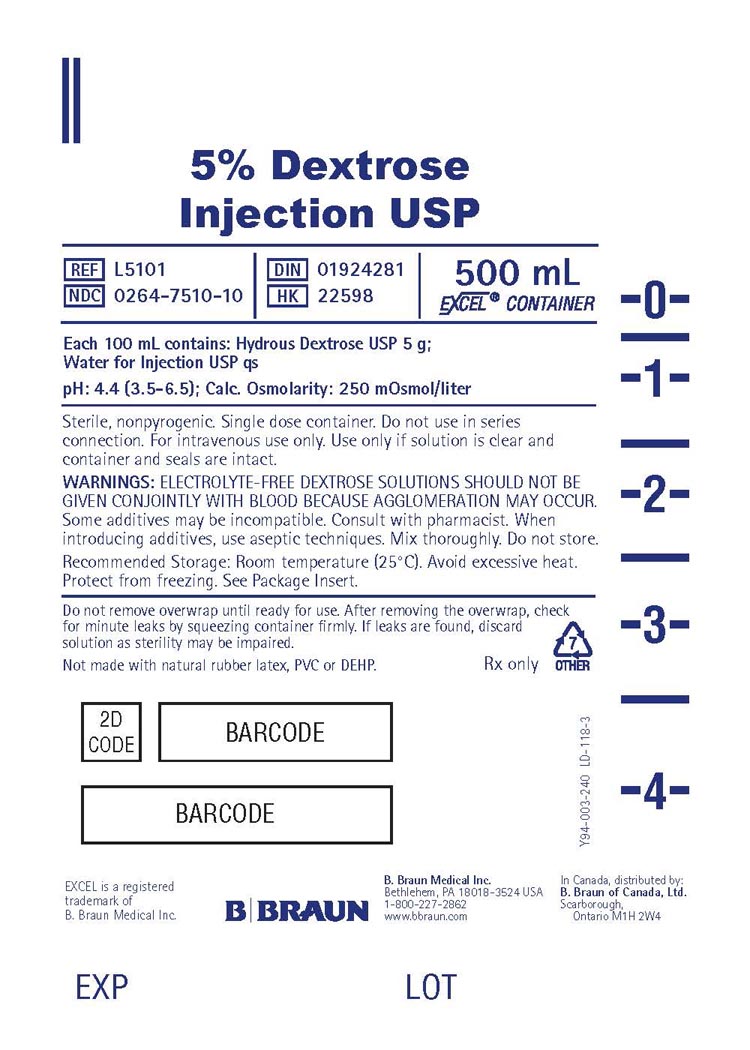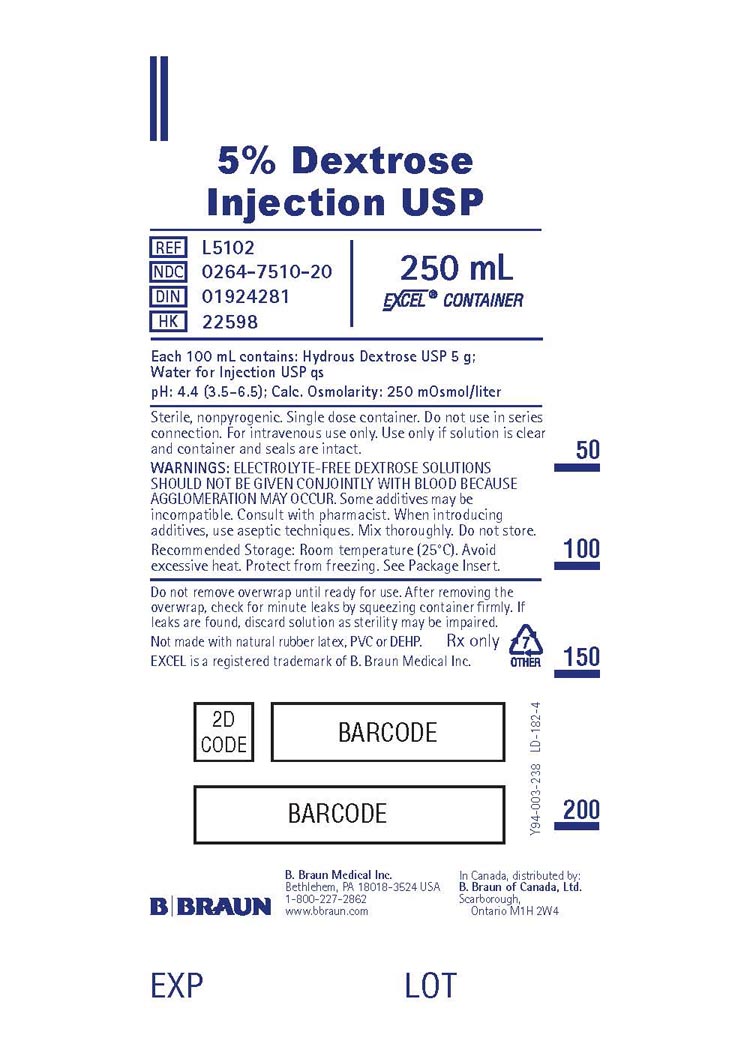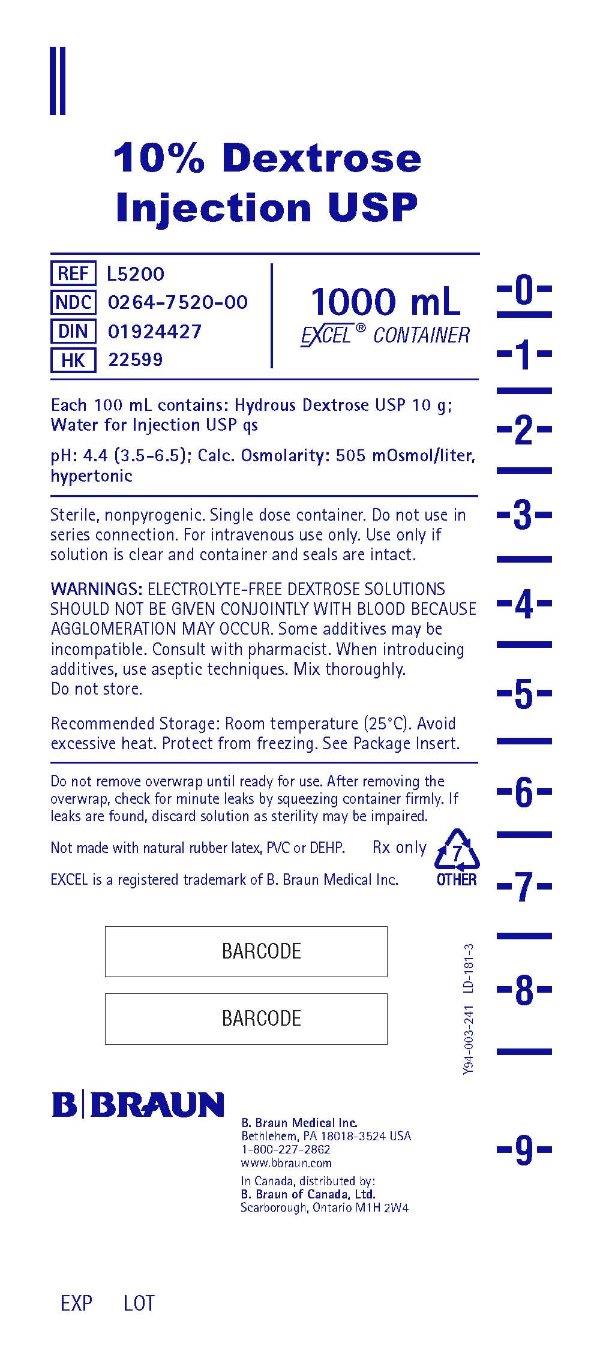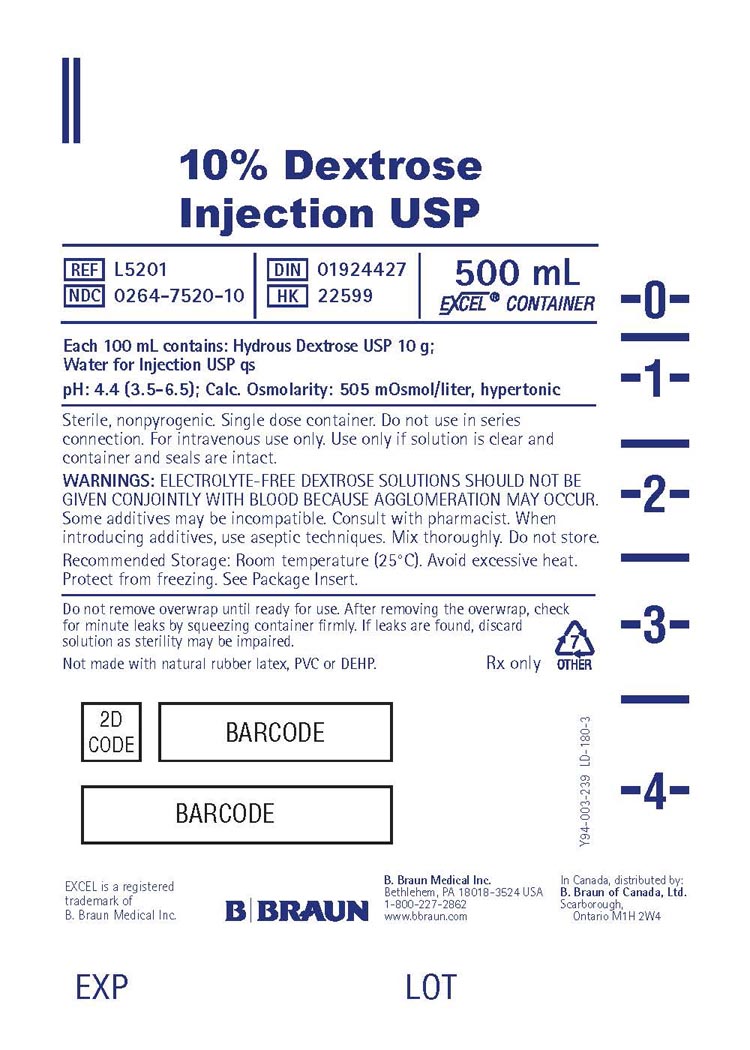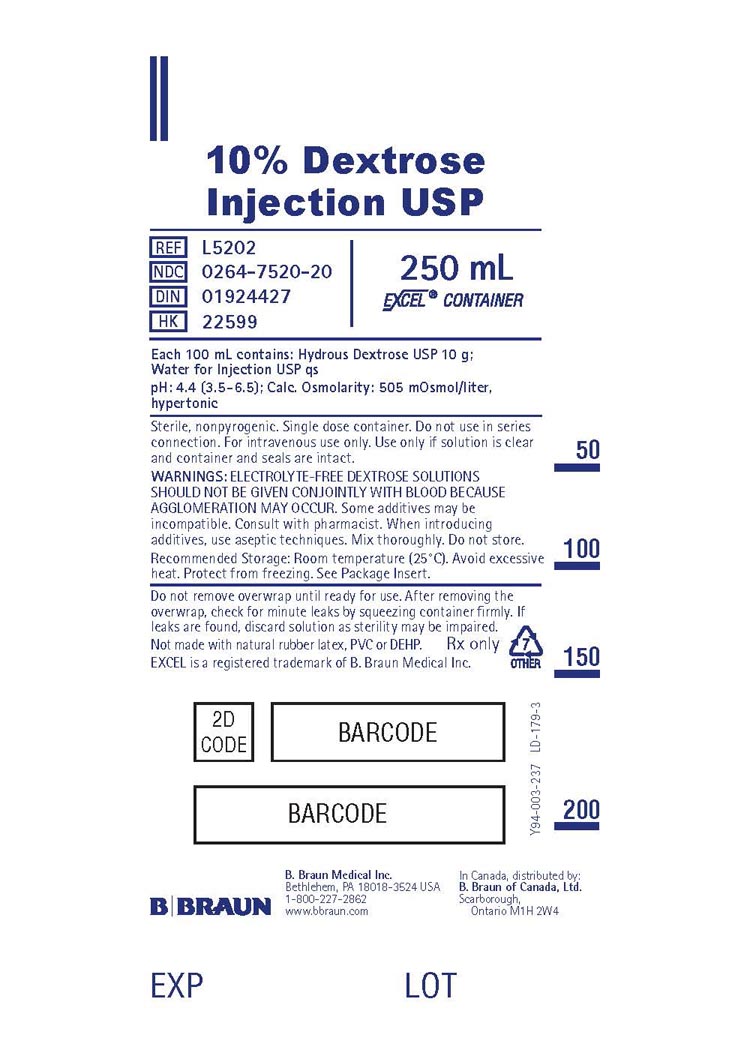 DRUG LABEL: DEXTROSE
NDC: 0264-7510 | Form: SOLUTION
Manufacturer: B. Braun Medical Inc.
Category: prescription | Type: HUMAN PRESCRIPTION DRUG LABEL
Date: 20240312

ACTIVE INGREDIENTS: DEXTROSE, UNSPECIFIED FORM 5 g/100 mL
INACTIVE INGREDIENTS: WATER

Dextrose Injections USP

DESCRIPTION

Each 100 mL of 5% Dextrose Injection USP contains:
Hydrous Dextrose USP 5 g; Water for Injection USP qs
pH: 4.4 (3.5–6.5); Calculated Osmolarity: 250 mOsmol/liter
Calories per liter: 170

Each 100 mL of 10% Dextrose Injection USP contains:
Hydrous Dextrose USP 10 g; Water for Injection USP qs
pH: 4.4 (3.5–6.5); Calculated Osmolarity: 505 mOsmol/liter, hypertonic
Calories per liter: 340

Dextrose Injections USP are sterile, nonpyrogenic and contain no bacteriostatic or antimicrobial agents. These products are intended for intravenous administration.

The formula of the active ingredient is:

Ingredient | Molecular Formula | Molecular Weight
Hydrous Dextrose USP |  | 198.17

Not made with natural rubber latex, PVC or DEHP.

The plastic container is made from a multilayered film specifically developed for parenteral drugs. It contains no plasticizers and exhibits virtually no leachables. The solution contact layer is a rubberized copolymer of ethylene and propylene. The container is nontoxic and biologically inert. The container-solution unit is a closed system and is not dependent upon entry of external air during administration. The container is overwrapped to provide protection from the physical environment and to provide an additional moisture barrier when necessary.

Addition of medication should be accomplished using complete aseptic technique.

The closure system has two ports; the one for the administration set has a tamper evident plastic protector and the other is a medication addition site. Refer to the Directions for Use of the container.

CLINICAL PHARMACOLOGY

Dextrose Injections USP provide calories and are a source of water for hydration. They are capable of inducing diuresis depending on the clinical condition of the patient.

Dextrose is readily metabolized, may decrease losses of body protein and nitrogen, promotes glycogen deposition and decreases or prevents ketosis if sufficient doses are provided.

Water is an essential constituent of all body tissues and accounts for approximately 70% of total body weight. Average normal adult daily requirements range from two to three liters (1.0 to 1.5 liters each for insensible water loss by perspiration and urine production).

INDICATIONS AND USAGE

These intravenous solutions are indicated for use in adults and pediatric patients as sources of calories and water for hydration.

CONTRAINDICATIONS

Solutions containing dextrose may be contraindicated in patients with hypersensitivity to corn products.

WARNINGS

The administration of intravenous solutions can cause fluid and/or solute overload resulting in dilution of serum electrolyte concentrations, overhydration, congested states or pulmonary edema. The risk of dilutional states is inversely proportional to the electrolyte concentration.

WARNING: Dextrose Injection USP contains aluminum that may be toxic. Aluminum may reach toxic levels with prolonged parenteral administration if kidney function is impaired. Premature neonates are particularly at risk because their kidneys are immature, and they require large amounts of calcium and phosphate solutions, which contain aluminum.

Research indicates that patients with impaired kidney function, including premature neonates, who receive parenteral levels of aluminum at greater than 4 to 5 mcg/kg/day accumulate aluminum at levels associated with central nervous system and bone toxicity. Tissue loading may occur at even lower rates of administration.

Prolonged infusion of isotonic or hypotonic dextrose in water may increase the volume of extracellular fluid and cause water intoxication.

Solutions containing dextrose without electrolytes should not be administered simultaneously with blood through the same infusion set because of the possibility of agglomeration.

Excessive administration of potassium-free dextrose solutions may result in significant hypokalemia. Serum potassium levels should be maintained and potassium supplemented as required.

In very low birth weight infants, excessive or rapid administration of dextrose injection may result in increased serum osmolality and possible intracerebral hemorrhage.

PRECAUTIONS

General

These solutions should be used with care in patients with hypervolemia, renal insufficiency, urinary tract obstruction, or impending or frank cardiac decompensation.

Solutions containing dextrose should be used with caution in patients with overt or known subclinical diabetes mellitus or carbohydrate intolerance for any reason.

Essential electrolytes, minerals, and vitamins should be supplied as needed.

Hypokalemia may develop during parenteral administration of hypertonic dextrose solutions. Sufficient amounts of potassium should be added to dextrose solutions administered to fasting patients with good renal function, especially those on digitalis therapy.

To minimize the risk of possible incompatibilities arising from mixing this solution with other additives that may be prescribed, the final infusate should be inspected for cloudiness or precipitation immediately after mixing, prior to administration, and periodically during administration.

Do not use plastic containers in series connection.

If administration is controlled by a pumping device, care must be taken to discontinue pumping action before the container runs dry or air embolism may result. If administration is not controlled by a pumping device, refrain from applying excessive pressure (>300mmHg) causing distortion to the container such as wringing or twisting. Such handling could result in breakage of the container.

These solutions are intended for intravenous administration using sterile equipment. It is recommended that intravenous administration apparatus be replaced at least once every 24 hours.

Use only if solution is clear and container and seals are intact.

Dextrose Injection USP contains no more than 25 mcg/L of aluminum.

Laboratory Tests

Clinical evaluation and periodic laboratory determinations are necessary to monitor changes in fluid balance, electrolyte concentrations, and acid-base balance during prolonged parenteral therapy or whenever the condition of the patient warrants such evaluation. Significant deviations from normal concentrations may require tailoring of the electrolyte pattern, in these or alternative solutions.

Drug Interactions

Some additives may be incompatible. Consult with pharmacist. When introducing additives, use aseptic techniques. Mix thoroughly. Do not store.

Carcinogenesis, Mutagenesis, Impairment of Fertility

Studies with Dextrose Injections USP have not been performed to evaluate carcinogenic potential, mutagenic potential or effects on fertility.

Pregnancy

Teratogenic Effects

Animal reproduction studies have not been conducted with Dextrose Injections USP. It is also not known whether Dextrose Injections USP can cause fetal harm when administered to a pregnant woman or can affect reproduction capacity. Dextrose Injections USP should be given to a pregnant woman only if clearly needed.

Labor and Delivery

As reported in the literature, dextrose solutions have been administered during labor and delivery. Caution should be exercised, and the fluid balance, glucose and electrolyte concentrations and acid-base balance, of both mother and fetus should be evaluated periodically or whenever warranted by the condition of the patient or fetus.

Nursing Mothers

Because many drugs are excreted in human milk, caution should be exercised when Dextrose Injections USP are administered to a nursing woman.

Pediatric Use

In neonates or in very small infants even small volumes of fluid may affect fluid and electrolyte balance. Care must be exercised in treatment of neonates, especially pre-term neonates, whose renal function may be immature and whose ability to excrete fluid and solute loads may be limited. Fluid intake, urine output, and serum electrolytes should be monitored closely.

Serum glucose concentrations should be frequently monitored when dextrose is prescribed to pediatric patients, particularly infants, neonates, and low birth weight infants.

See WARNINGS and DOSAGE AND ADMINISTRATION.

Geriatric Use

An evaluation of current literature revealed no clinical experience identifying differences in responses between the elderly and younger patients. In general, dose selection for an elderly patient should be cautious, usually starting at the low end of the dosing range, reflecting the greater frequency of decreased hepatic, renal, or cardiac function, and of concomitant disease or other drug therapy.

These drugs are known to be substantially excreted by the kidney, and the risk of toxic reactions to these drugs may be greater in patients with impaired renal function. Because elderly patients are more likely to have decreased renal function, care should be taken in dose selection, and it may be useful to monitor renal function.

See WARNINGS.

ADVERSE REACTIONS

Reactions which may occur because of the solution or the technique of administration include febrile response, infection at the site of injection, venous thrombosis or phlebitis extending from the site of injection, extravasation and hypervolemia.

Too rapid infusion of hypertonic solutions may cause local pain and venous irritation. Rate of administration should be adjusted according to tolerance. Use of the largest peripheral vein and a small bore needle is recommended. (See DOSAGE AND ADMINISTRATION.)

The physician should also be alert to the possibility of adverse reactions to drug additives. Prescribing information for drug additives to be administered in this manner should be consulted.

If an adverse reaction does occur, discontinue the infusion, evaluate the patient, institute appropriate therapeutic countermeasures, and save the remainder of the fluid for examination if deemed necessary.

OVERDOSAGE

In the event of a fluid or solute overload during parenteral therapy, reevaluate the patient's condition and institute appropriate corrective treatment.

DOSAGE AND ADMINISTRATION

These solutions are for intravenous use only.

Dosage is to be directed by a physician and is dependent upon age, weight, clinical condition of the patient and laboratory determinations. Frequent laboratory determinations and clinical evaluation are essential to monitor changes in blood glucose and electrolyte concentrations, and fluid and electrolyte balance during prolonged parenteral therapy.

When a hypertonic solution is to be administered peripherally, it should be slowly infused through a small bore needle, placed well within the lumen of a large vein to minimize venous irritation. Carefully avoid infiltration.

Fluid administration should be based on calculated maintenance or replacement fluid requirements for each patient.

Some additives may be incompatible. Consult with pharmacist. When introducing additives, use aseptic techniques. Mix thoroughly. Do not store.

Parenteral drug products should be inspected visually for particulate matter and discoloration prior to administration, whenever solution and container permit.

Pediatric Use

There is no specific pediatric dose. The dose is dependent on weight, clinical condition, and laboratory results. Follow recommendations of appropriate pediatric reference text. (See WARNINGS and PRECAUTIONS.)

HOW SUPPLIED

Dextrose Injections USP are supplied sterile and nonpyrogenic in EXCEL® Containers. The 1000 mL containers are packaged 12 per case, the 500 mL and 250 mL containers are packaged 24 per case.

NDC | REF | Size
5% Dextrose Injection USP (Canada DIN 01924281)
0264-7510-00 | L5100 | 1000 mL
0264-7510-10 | L5101 | 500 mL
0264-7510-20 | L5102 | 250 mL
10% Dextrose Injection USP (Canada DIN 01924427)
0264-7520-00 | L5200 | 1000 mL
0264-7520-10 | L5201 | 500 mL
0264-7520-20 | L5202 | 250 mL

STORAGE AND HANDLING

Exposure of pharmaceutical products to heat should be minimized. Avoid excessive heat. Protect from freezing. It is recommended that the product be stored at room temperature (25°C); however, brief exposure up to 40°C does not adversely affect the product.

Rx only

Revised: May 2019

EXCEL is a registered trademark of B. Braun Medical Inc.

Directions for Use of EXCEL® Container

Caution: Do not use plastic containers in series connection.

To Open

Tear overwrap down at notch and remove solution container. Check for minute leaks by squeezing solution container firmly. If leaks are found, discard solution as sterility may be impaired. If supplemental medication is desired, follow directions below before preparing for administration.

NOTE: Before use, perform the following checks:

Inspect each container. Read the label. Ensure solution is the one ordered and is within the expiration date.

Invert container and carefully inspect the solution in good light for cloudiness, haze, or particulate matter. Any container which is suspect should not be used.

Use only if solution is clear and container and seals are intact.

Preparation for Administration

1. Remove plastic protector from sterile set port at bottom of container.
2. Attach administration set. Refer to complete directions accompanying set.

To Add Medication

Warning: Some additives may be incompatible.

To Add Medication Before Solution Administration

1. Prepare medication site.
2. Using syringe with 18–22 gauge needle, puncture medication port and inner diaphragm and inject.
3. Squeeze and tap ports while ports are upright and mix solution and medication thoroughly.

To Add Medication During Solution Administration

1. Close clamp on the set.
2. Prepare medication site.
3. Using syringe with 18–22 gauge needle of appropriate length (at least 5/8 inch), puncture resealable medication port and inner diaphragm and inject.
4. Remove container from IV pole and/or turn to an upright position.
5. Evacuate both ports by tapping and squeezing them while container is in the upright position.
6. Mix solution and medication thoroughly.
7. Return container to in use position and continue administration.

B. Braun Medical Inc.
Bethlehem, PA 18018-3524 USA
1-800-227-2862
www.bbraun.com

In Canada, distributed by:
B. Braun of Canada, Ltd.
Scarborough, Ontario M1H 2W4

Y36-002-996 LD-498-3

PRINCIPAL DISPLAY PANEL - 1000 mL Container Label

5% Dextrose
Injection USP

REF L5100
NDC 0264-7510-00
DIN 01924281
HK 22598

1000 mL
EXCEL® CONTAINER

Each 100 mL contains: Hydrous Dextrose USP 5 g;
Water for Injection USP qs

pH: 4.4 (3.5-6.5); Calc. Osmolarity: 250 mOsmol/liter

Sterile, nonpyrogenic. Single dose container. Do not use in
series connection. For intravenous use only. Use only if
solution is clear and container and seals are intact.

WARNINGS: ELECTROLYTE-FREE DEXTROSE SOLUTIONS
SHOULD NOT BE GIVEN CONJOINTLY WITH BLOOD BECAUSE
AGGLOMERATION MAY OCCUR. Some additives may be
incompatible. Consult with pharmacist. When introducing
additives, use aseptic techniques. Mix thoroughly.
Do not store.

Recommended Storage: Room temperature (25°C). Avoid
excessive heat. Protect from freezing. See Package Insert.

Do not remove overwrap until ready for use. After removing the
overwrap, check for minute leaks by squeezing container firmly. If
leaks are found, discard solution as sterility may be impaired.

Not made with natural rubber latex, PVC or DEHP.

Rx only

EXCEL is a registered trademark of B. Braun Medical Inc.

7
OTHER

B. Braun Medical Inc.
Bethlehem, PA 18018-3524 USA
1-800-227-2862
www.bbraun.com

In Canada, distributed by:
B. Braun of Canada, Ltd.
Scarborough, Ontario M1H 2W4

Y94-003-242
LD-111-3

EXP

LOT

PRINCIPAL DISPLAY PANEL - 500 mL Container Label

5% Dextrose Injection USP

REF L5101
NDC 0264-7510-10

DIN 01924281
HK 22598

500 mL
EXCEL® CONTAINER

Each 100 mL contains: Hydrous Dextrose USP 5 g;
Water for Injection USP qs
pH: 4.4 (3.5-6.5); Calc. Osmolarity: 250 mOsmol/liter

Sterile, nonpyrogenic. Single dose container. Do not use in series
connection. For intravenous use only. Use only if solution is clear and
container and seals are intact.

WARNINGS: ELECTROLYTE-FREE DEXTROSE SOLUTIONS SHOULD NOT BE
GIVEN CONJOINTLY WITH BLOOD BECAUSE AGGLOMERATION MAY OCCUR.
Some additives may be incompatible. Consult with pharmacist. When
introducing additives, use aseptic techniques. Mix thoroughly. Do not store.

Recommended Storage: Room temperature (25°C). Avoid excessive heat.
Protect from freezing. See Package Insert.

Do not remove overwrap until ready for use. After removing the overwrap, check
for minute leaks by squeezing container firmly. If leaks are found, discard
solution as sterility may be impaired.

Not made with natural rubber latex, PVC or DEHP.

Rx only

7
OTHER

EXCEL is a registered trademark of B. Braun Medical Inc.

B. Braun Medical Inc.
Bethlehem, PA 18018-3524 USA
1-800-227-2862
www.bbraun.com

In Canada, distributed by:
B. Braun of Canada, Ltd.
Scarborough, Ontario M1H 2W4

Y94-003-240
LD-118-3

EXP

LOT

Y94-003-240

PRINCIPAL DISPLAY PANEL - 250 mL Container Label

5% Dextrose
Injection USP

REF L5102
NDC 0264-7510-20
DIN 01924281
HK 22598

250 mL
EXCEL® CONTAINER

Each 100 mL contains: Hydrous Dextrose USP 5 g;
Water for Injection USP qs

pH: 4.4 (3.5-6.5); Calc. Osmolarity: 250 mOsmol/liter

Sterile, nonpyrogenic. Single dose container. Do not use in series
connection. For intravenous use only. Use only if solution is clear
and container and seals are intact.

WARNINGS: ELECTROLYTE-FREE DEXTROSE SOLUTIONS
SHOULD NOT BE GIVEN CONJOINTLY WITH BLOOD BECAUSE
AGGLOMERATION MAY OCCUR. Some additives may be
incompatible. Consult with pharmacist. When introducing
additives, use aseptic techniques. Mix thoroughly. Do not store.

Recommended Storage: Room temperature (25°C). Avoid
excessive heat. Protect from freezing. See Package Insert.

Do not remove overwrap until ready for use. After removing the
overwrap, check for minute leaks by squeezing container firmly. If
leaks are found, discard solution as sterility may be impaired.

Not made with natural rubber latex, PVC or DEHP.

Rx only

EXCEL is a registered trademark of B. Braun Medical Inc.

7
OTHER

B. Braun Medical Inc.
Bethlehem, PA 18018-3524 USA
1-800-227-2862
www.bbraun.com

In Canada, distributed by:
B. Braun of Canada, Ltd.
Scarborough, Ontario M1H 2W4

Y94-003-238
LD-182-4

EXP

LOT

Y94-003-238

PRINCIPAL DISPLAY PANEL - 1000 mL Container Label

10% Dextrose
Injection USP

REF L5200
NDC 0264-7520-00
DIN 01924427
HK 22599

1000 mL
EXCEL® CONTAINER

Each 100 mL contains: Hydrous Dextrose USP 10 g;
Water for Injection USP qs

pH: 4.4 (3.5-6.5); Calc. Osmolarity: 505 mOsmol/liter,
hypertonic

Sterile, nonpyrogenic. Single dose container. Do not use in
series connection. For intravenous use only. Use only if
solution is clear and container and seals are intact.

WARNINGS: ELECTROLYTE-FREE DEXTROSE SOLUTIONS
SHOULD NOT BE GIVEN CONJOINTLY WITH BLOOD BECAUSE
AGGLOMERATION MAY OCCUR. Some additives may be
incompatible. Consult with pharmacist. When introducing
additives, use aseptic techniques. Mix thoroughly.
Do not store.

Recommended Storage: Room temperature (25°C). Avoid
excessive heat. Protect from freezing. See Package Insert.

Do not remove overwrap until ready for use. After removing the
overwrap, check for minute leaks by squeezing container firmly. If
leaks are found, discard solution as sterility may be impaired.

Not made with natural rubber latex, PVC or DEHP.

Rx only

EXCEL is a registered trademark of B. Braun Medical Inc.

7
OTHER

B. Braun Medical Inc.
Bethlehem, PA 18018-3524 USA
1-800-227-2862
www.bbraun.com

In Canada, distributed by:
B. Braun of Canada, Ltd.
Scarborough, Ontario M1H 2W4

Y94-003-241
LD-181-3

EXP

LOT

PRINCIPAL DISPLAY PANEL - 500 mL Container Label

10% Dextrose Injection USP

REF L5201
NDC 0264-7520-10

DIN 01924427
HK 22599

500 mL
EXCEL® CONTAINER

Each 100 mL contains: Hydrous Dextrose USP 10 g;
Water for Injection USP qs

pH: 4.4 (3.5-6.5); Calc. Osmolarity: 505 mOsmol/liter, hypertonic

Sterile, nonpyrogenic. Single dose container. Do not use in series
connection. For intravenous use only. Use only if solution is clear and
container and seals are intact.

WARNINGS: ELECTROLYTE-FREE DEXTROSE SOLUTIONS SHOULD NOT BE
GIVEN CONJOINTLY WITH BLOOD BECAUSE AGGLOMERATION MAY OCCUR.
Some additives may be incompatible. Consult with pharmacist. When
introducing additives, use aseptic techniques. Mix thoroughly. Do not store.

Recommended Storage: Room temperature (25°C). Avoid excessive heat.
Protect from freezing. See Package Insert.

Do not remove overwrap until ready for use. After removing the overwrap, check
for minute leaks by squeezing container firmly. If leaks are found, discard
solution as sterility may be impaired.

Not made with natural rubber latex, PVC or DEHP.

Rx only

EXCEL is a registered trademark of B. Braun Medical Inc.

7
OTHER

B. Braun Medical Inc.
Bethlehem, PA 18018-3524 USA
1-800-227-2862
www.bbraun.com

In Canada, distributed by:
B. Braun of Canada, Ltd.
Scarborough, Ontario M1H 2W4

Y94-003-239
LD-180-3

EXP

LOT

Y94-003-239

PRINCIPAL DISPLAY PANEL - 250 mL Container Label

10% Dextrose
Injection USP

REF L5202
NDC 0264-7520-20
DIN 01924427
HK 22599

250 mL
EXCEL® CONTAINER

Each 100 mL contains: Hydrous Dextrose USP 10 g;
Water for Injection USP qs

pH: 4.4 (3.5-6.5); Calc. Osmolarity: 505 mOsmol/liter,
hypertonic

Sterile, nonpyrogenic. Single dose container. Do not use in series
connection. For intravenous use only. Use only if solution is clear
and container and seals are intact.

WARNINGS: ELECTROLYTE-FREE DEXTROSE SOLUTIONS
SHOULD NOT BE GIVEN CONJOINTLY WITH BLOOD BECAUSE
AGGLOMERATION MAY OCCUR. Some additives may be
incompatible. Consult with pharmacist. When introducing
additives, use aseptic techniques. Mix thoroughly. Do not store.

Recommended Storage: Room temperature (25°C). Avoid excessive
heat. Protect from freezing. See Package Insert.

Do not remove overwrap until ready for use. After removing
the overwrap, check for minute leaks by squeezing container firmly. If
leaks are found, discard solution as sterility may be impaired.

Not made with natural rubber latex, PVC or DEHP.

Rx only

EXCEL is a registered trademark of B. Braun Medical Inc.

7
OTHER

B. Braun Medical Inc.
Bethlehem, PA 18018-3524 USA
1-800-227-2862
www.bbraun.com

In Canada, distributed by:
B. Braun of Canada, Ltd.
Scarborough, Ontario M1H 2W4

Y94-003-237
LD-179-3

EXP

LOT

Y94-003-237